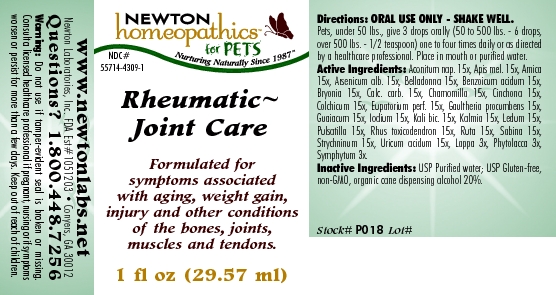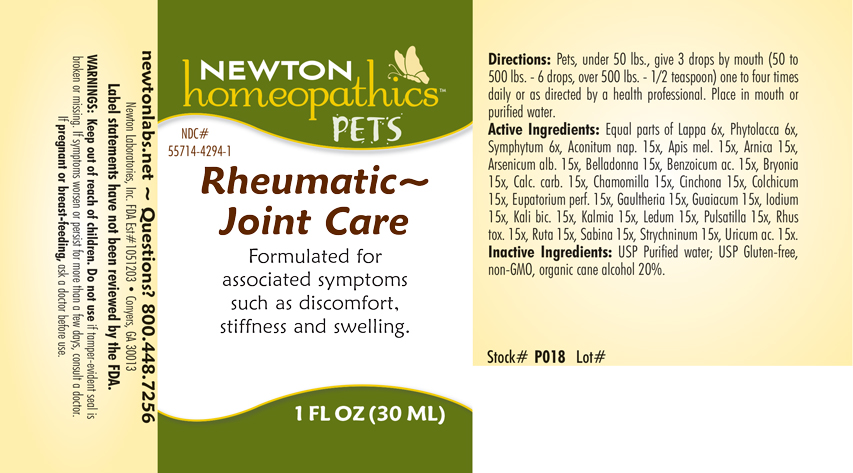 DRUG LABEL: Rheumatic - Joint Care
NDC: 55714-4294 | Form: LIQUID
Manufacturer: Newton Laboratories, Inc.
Category: homeopathic | Type: OTC ANIMAL DRUG LABEL
Date: 20211022

ACTIVE INGREDIENTS: Aconitum Napellus 15 [hp_X]/1 mL; Apis Mellifera 15 [hp_X]/1 mL; Arnica Montana 15 [hp_X]/1 mL; Arsenic Trioxide 15 [hp_X]/1 mL; Atropa Belladonna 15 [hp_X]/1 mL; Benzoic Acid 15 [hp_X]/1 mL; Bryonia Alba Root 15 [hp_X]/1 mL; Oyster Shell Calcium Carbonate, Crude 15 [hp_X]/1 mL; Matricaria Recutita 15 [hp_X]/1 mL; Cinchona Officinalis Bark 15 [hp_X]/1 mL; Colchicum Autumnale Bulb 15 [hp_X]/1 mL; Eupatorium Perfoliatum Flowering Top 15 [hp_X]/1 mL; Gaultheria Procumbens Top 15 [hp_X]/1 mL; Guaiac 15 [hp_X]/1 mL; Iodine 15 [hp_X]/1 mL; Potassium Dichromate 15 [hp_X]/1 mL; Kalmia Latifolia Leaf 15 [hp_X]/1 mL; Ledum Palustre Twig 15 [hp_X]/1 mL; Pulsatilla Vulgaris 15 [hp_X]/1 mL; Toxicodendron Pubescens Leaf 15 [hp_X]/1 mL; Ruta Graveolens Flowering Top 15 [hp_X]/1 mL; Juniperus Sabina Leafy Twig 15 [hp_X]/1 mL; Strychnine 15 [hp_X]/1 mL; Uric Acid 15 [hp_X]/1 mL; Arctium Lappa Root 6 [hp_X]/1 mL; Phytolacca Americana Root 6 [hp_X]/1 mL; Comfrey Root 6 [hp_X]/1 mL
INACTIVE INGREDIENTS: Alcohol; Water

Rheumatic - Joint Care

INDICATIONS & USAGE SECTION

Formulated for associated symptoms such as discomfort, stiffness and swelling.

DOSAGE & ADMINISTRATION SECTION

Directions: Pets, under 50 lbs., give 3 drops by mouth (50 to 500 lbs. - 6 drops, over 500 lbs. - 1/2 teaspoon) one to four times daily or as directed by a health professional. Place in mouth or purified water.

OTC - ACTIVE INGREDIENT SECTION

Equal parts of Lappa 6x, Phytolacca 6x, Symphytum 6x, Aconitum nap. 15x, Apis mel. 15x, Arnica 15x, Arsenicum alb. 15x, Belladonna 15x, Benzoicum acidum 15x, Bryonia 15x, Calc. carb. 15x, Chamomilla 15x, Cinchona 15x, Colchicum 15x, Eupatorium perf. 15x, Gaultheria 5x, Guaiacum 15x, Iodium 15x, Kali bic. 15x, Kalmia 15x, Ledum 15x, Pulsatilla 15x, Rhus tox. 15x, Ruta 15x, Sabina 15x, Strychninum 15x, Uricum acidum 15x.

OTC - PURPOSE SECTION

Formulated for associated symptoms such as discomfort, stiffness and swelling.

INACTIVE INGREDIENT SECTION

Inactive Ingredients: USP Purified Water; USP Gluten-free, non-GMO, organic cane alcohol 20%.

QUESTIONS SECTION

newtonlabs.net Questions? 800.448.7256
Newton Laboratories, Inc. FDA Est # 1051203 - Conyers, GA 30013

WARNINGS SECTION

Warnings: Keep out of reach of children. Do not use if tamper-evident seal is broken or missing. If symptoms worsen or persist for more than a few days, consult a doctor. if pregnant or breast-feeding, ask a doctor before use.

OTC - PREGNANCY OR BREAST FEEDING SECTION

If pregnant or breast-feeding, ask a doctor before use.

OTC - KEEP OUT OF REACH OF CHILDREN SECTION

Keep out of reach of children.